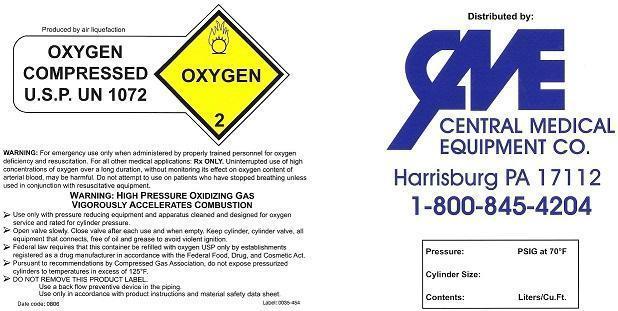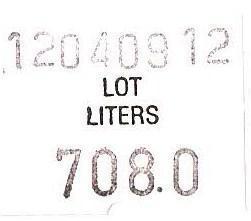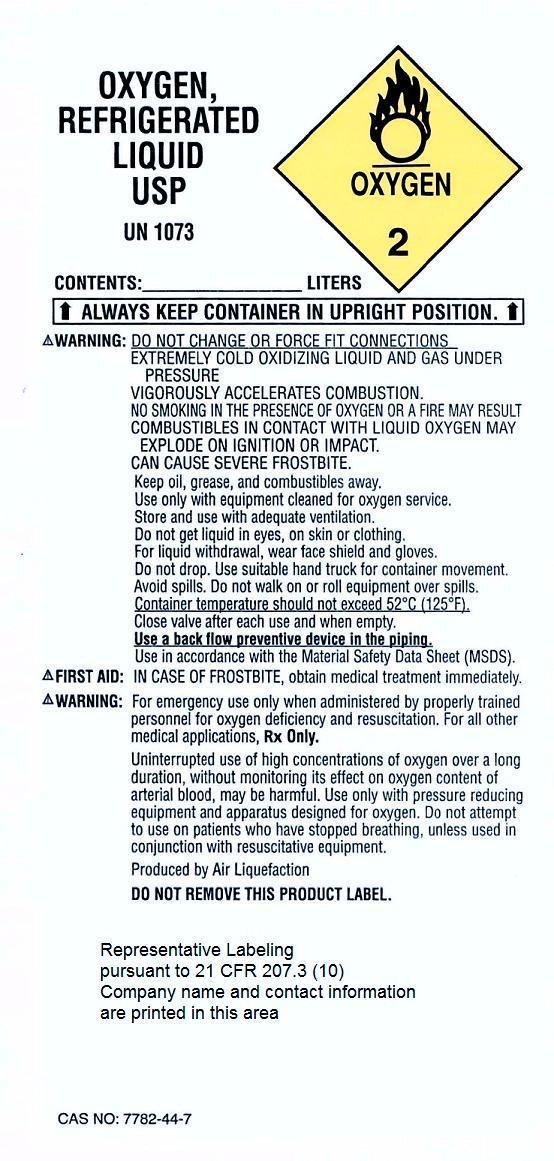 DRUG LABEL: Oxygen
NDC: 63577-035 | Form: GAS
Manufacturer: Central Medical Equipment Co.
Category: prescription | Type: HUMAN PRESCRIPTION DRUG LABEL
Date: 20140514

ACTIVE INGREDIENTS: Oxygen 99 L/100 L

Oxygen